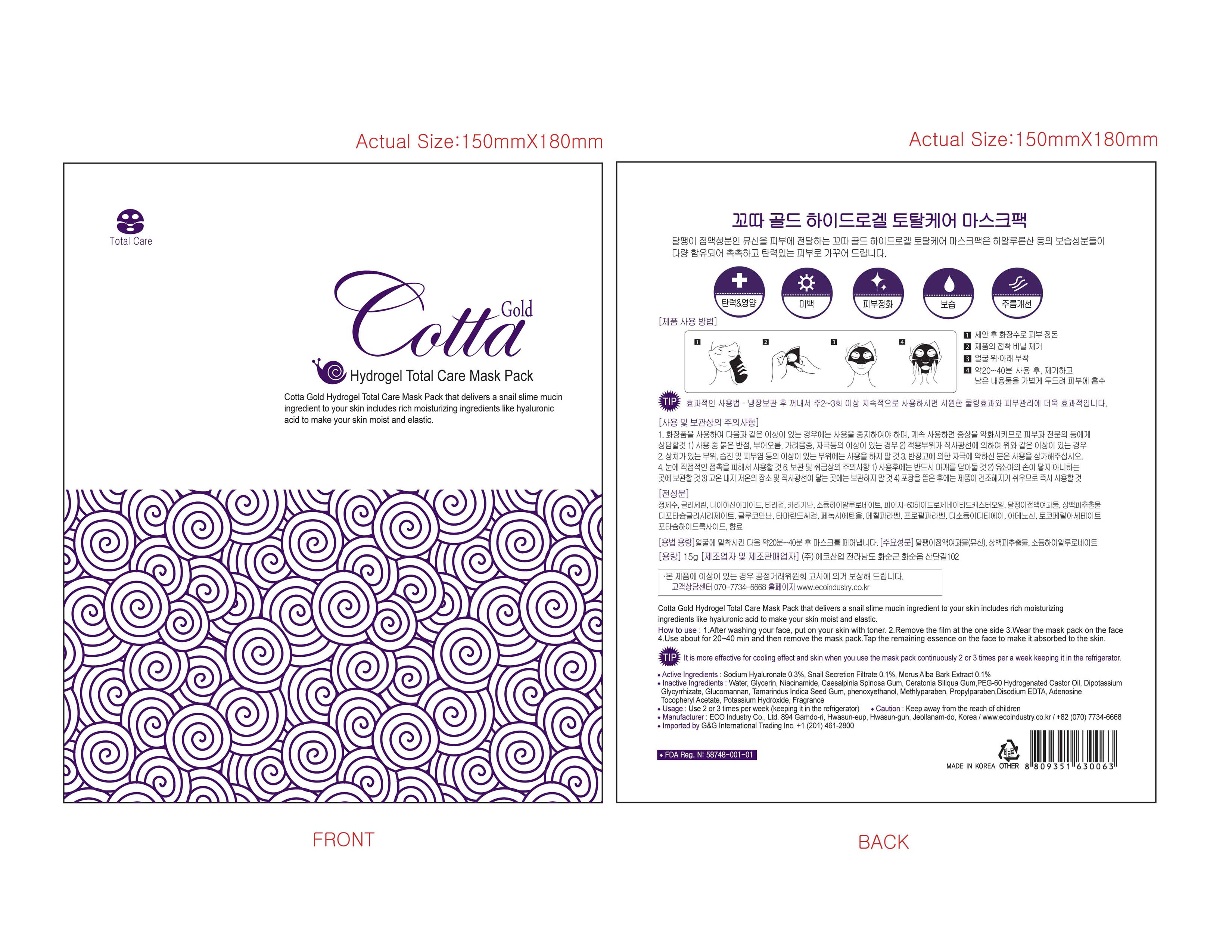 DRUG LABEL: Cotta
                
NDC: 58748-001 | Form: FILM, EXTENDED RELEASE
Manufacturer: ECO INDUSTRY CO., LTD
Category: otc | Type: HUMAN OTC DRUG LABEL
Date: 20130708

ACTIVE INGREDIENTS: HYALURONATE SODIUM .3 g/100 g; GARDEN SNAIL MUCIN .1 g/100 g; MORUS ALBA ROOT BARK  .1 g/100 g
INACTIVE INGREDIENTS: WATER; GLYCERIN; NIACINAMIDE; CAESALPINIA SPINOSA RESIN; LOCUST BEAN GUM; PEG-60 HYDROGENATED CASTOR OIL; GLYCYRRHIZINATE DIPOTASSIUM; KONJAC MANNAN; TAMARIND SEED; PHENOXYETHANOL; METHYLPARABEN; PROPYLPARABEN; EDETATE DISODIUM; ADENOSINE; .ALPHA.-TOCOPHEROL ACETATE; POTASSIUM HYDROXIDE

Drug Facts

INACTIVE INGREDIENT

Inactive Ingredients Water, Glycerin, Niacinamide, Caesalpinia Spinosa Gum,

Ceratonia Siliqua Gum, Peg-60 Hydrogenated Castor Oil, Dipotassium Glycyrrhizate,

Glucomannan, Tamarindus Indica Seed Gum, phenoxyethanol, Methyparaben,

Propylparaben, Disodium EDTA, Adenosinine, Tocopheryl Acetate,

Potassium Hydroxide, Fragrance

ACTIVE INGREDIENT

Active Ingredients Sodium Hyaluronate 0.3%, Snail Secretion Filtrate 0.1%, Morus Alba Bark Extract 0.1%

Caution: Keep away form the reach of children

DOSAGE AND ADMINISTRATION

How to Use: 1. After washing your face, put on your skin with toner. 2. Remove the film at the one side

3. Wear the mask pack on the face 4. Use for about 20-40 min and then remove the mask pack.

Tap the remaining essence on the face to make it absorbed to the skin.

INDICATIONS AND USAGE

Usage: Use 2 or 3 times per week (keeping it in the refrigerator)

Cotta Gold Hydrogel Total Care Mask Pack that delivers a snail slime mucin ingredient

to your skin includes rich moisturizing ingredients like hyalulonoic acid to make your

skin moist and elastic

PURPOSE

Cotta Gold Total Care Mask Pack that delivers a snail slime mulch ingredient to your skin includes rich moisturizing

ingredients like hyaluronic acid to make your skin moist and elastic

WARNINGS

Caution - Keep away from the reach of children